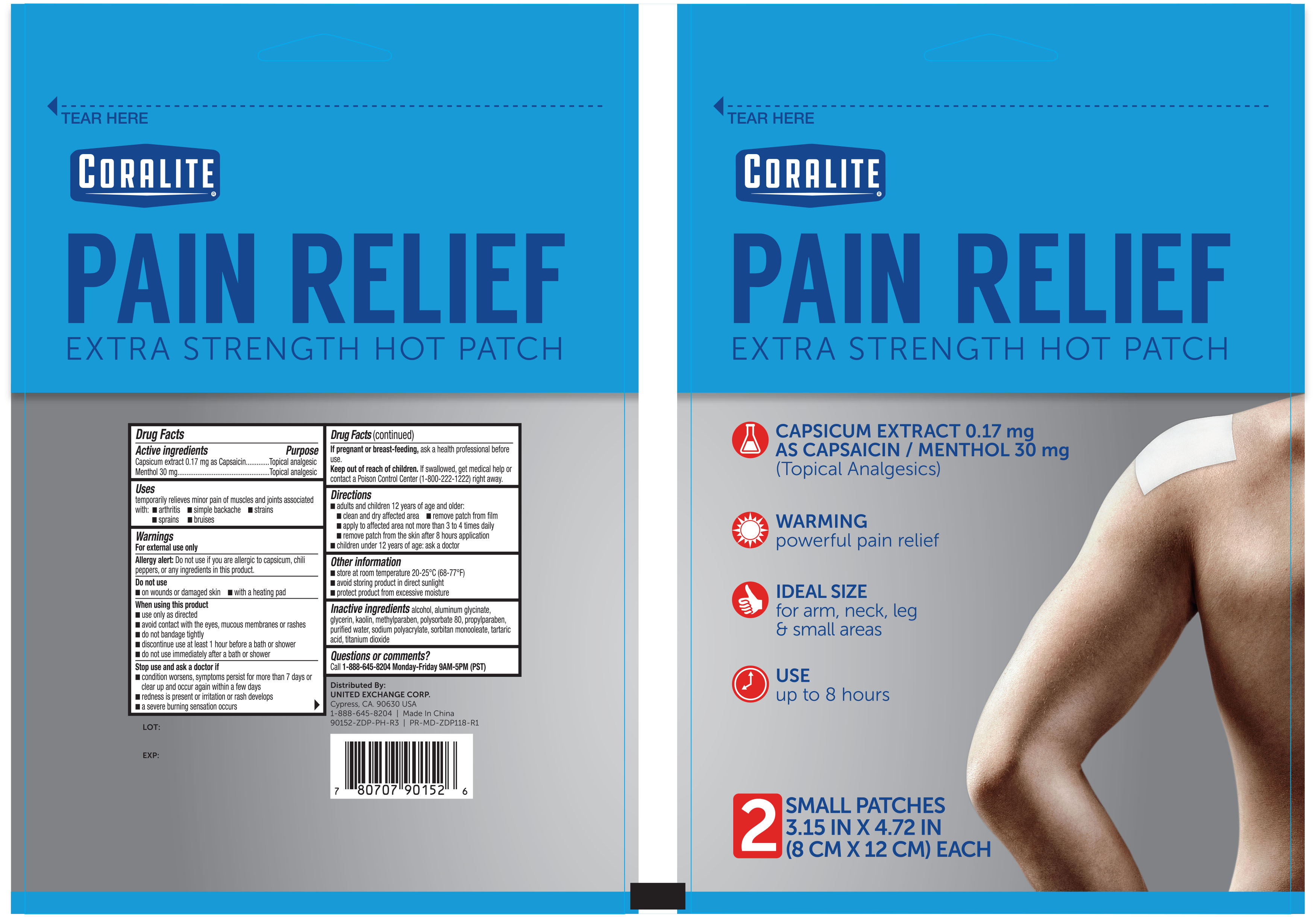 DRUG LABEL: Coralite Pain Relief Hot
NDC: 65923-146 | Form: PATCH
Manufacturer: United Exchange Corporation
Category: otc | Type: HUMAN OTC DRUG LABEL
Date: 20251023

ACTIVE INGREDIENTS: MENTHOL 30 mg/1 g; CAPSAICIN 0.83 mg/1 g
INACTIVE INGREDIENTS: TITANIUM DIOXIDE; GLYCERIN; ALCOHOL; TARTARIC ACID; METHYLPARABEN; POLYSORBATE 80; PROPYLPARABEN; WATER; DIHYDROXYALUMINUM AMINOACETATE ANHYDROUS; SODIUM POLYACRYLATE (2500000 MW); SORBITAN MONOOLEATE; KAOLIN

Coralite Pain Relief Extra Strength Hot Patch 2ct 90152 (90152, 2021)

Drug Facts

Active ingredient Purpose

Capsicum extract 0.17 mg as Capsaicin........Topical analgesic

Menthol 30 mg....................................................Topical analgesic

Uses

temporarily relieves minor pain of muscles and joints associated with:

- arthritis
- simple backache
- strains
- sprains
- bruises

Warnings

For external use only

Allergy alert: Do not use if you are allergic to capsicum, chili peppers, or any ingredients in this product.

Do not use

- on wounds or damaged skin
- with a heating pad

When using this product

- use only as directed
- avoid contact with the eyes, mucous membranes or rashes
- do not bandage tightly
- discontinue use at least 1 hour before a bath or shower
- do not use immediately after a bath or shower

Stop use and ask a doctor if

- condition worsens, symptoms persist for more than 7 days or clear up and occur again within a few days
- redness is present or irritation or rash develops
- a severe burning sensation occurs

PREGNANCY OR BREAST FEEDING

If pregnant or breast-feeding, ask a health professional before use.

Keep out of reach of children. If swallowed, get medical help or contact a Poison Control Center (1-800-222-1222) right away.

Directions

- adults and children 18 years of age and older:
- clean and dry affected area
- remove patch from film
- apply to affected area not more than 3 to 4 times daily
- removed patch from the skin after 8 hours application
- children under 12 years of age: ask a doctor

Other information

- store at room temperature 20-25°C (68-77°F)
- avoid storing product in direct sunlight
- protect product from excessive moisture

INACTIVE INGREDIENT

Inactive ingredients alcohol, aluminum glycinate, glycerin, kalin, methylparaben, polysorbate 80, propylparaben, purified water, sodium polyacrylate, sorbitan monooleate, tartaric acid, titanium dioxide

Questions or comments?

Call 1-800-814-8028 monday-Friday 9AM-5PM (PST)

DOSAGE AND ADMINISTRATION

Distributed By: UNITED EXCHANGE CORPORATION

Cypress, CA 90630 USA | 1-888-645-8204

Made In China